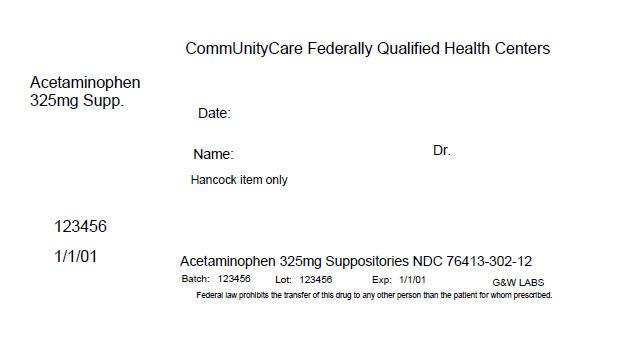 DRUG LABEL: ACEPHEN 
NDC: 76413-302 | Form: SUPPOSITORY
Manufacturer: Central Texas Community Health Centers
Category: otc | Type: HUMAN OTC DRUG LABEL
Date: 20160309

ACTIVE INGREDIENTS: Acetaminophen 325 mg/1 1
INACTIVE INGREDIENTS: Glyceryl Monostearate; Hydrogenated Coconut Oil; Peg-100 Stearate; Sorbitan Monooleate

AcephenTM Acetaminophen Suppositories USP
325 mg

ACTIVE INGREDIENT (in each rectal suppository)

Acetaminophen 325 mg

PURPOSE

Pain reliever/fever reducer

USES

temporarily
• reduces fever
• relieves minor aches, pains, and headache

WARNINGS

For rectal use only
Liver Warning: This product contains acetaminophen. Severe liver damage may occur if
• a child 6 to 12 years takes more than 5 doses in 24 hours
• an adult or child 12 years and older takes more than 6 doses in 24 hours, which is the maximum daily amount
• taken with other drugs containing acetaminophen
• an adult takes 3 or more alcoholic drinks every day while using this product
Allergy alert: acetaminophen may cause severe skin reactions. Symptoms may include:
• skin reddening
• blisters
• rash
If a skin reaction occurs, stop use and seek medical help right away.
Do not use
• in children under 6 years
• if you are allergic to acetaminophen
• with any other drug containing acetaminophen (prescription or nonprescription). If you are not sure whether a drug contains acetaminophen, ask a doctor or pharmacist.
Ask a doctor before use if
• you have liver disease
• you are taking the blood thinning drug warfarin
Stop use and ask a doctor if
• fever lasts more than 3 days (72 hours), or recurs
• new symptoms occur
• pain gets worse or lasts more than 10 days
• redness or swelling is present in the painful area
These may be signs of a serious condition.
If pregnant or breast-feeding, ask a health professional before use.
Keep out of reach of children. If swallowed or in case of overdose, get medical help or contact a Poison Control Center right away. Quick medical attention is critical in case of overdose for adults and for children even if you do not notice any signs or symptoms.

DIRECTIONS

• do not use more than directed
• remove foil wrapper
• insert suppository well up into rectum

children under 6 years | do not use
children 6-12 years | 1 suppository every 4 to 6 hours; (maximum of 5 doses in 24 hours)
adults and children; 12 years and older | 2 suppositories every 4 to 6 hours; (maximum of 6 doses)

Other Information

• store at room temperature 15˚-30˚C (59˚-86˚F)

INACTIVE INGREDIENTS

glyceryl stearate, hydrogenated vegetable oil, polyethylene glycol 100 stearate, sorbitan monooleate

QUESTIONS?

call 1-800-922-1038

PRINCIPAL DISPLAY PANEL - 325 mg Suppository Box Label

CommUnityCare Federally Qualified Health Centers

Acetaminophen
325mg Supp.

Date:

Name:
Dr.

Hancock item only

123456

1/1/01

Acetaminophen 325mg Suppositories NDC 76413-302-12

Batch: 123456
Lot: 123456
Exp: 1/1/01
G&W LABS

Federal law prohibits the transfer of this drug to any other person than the patient for whom prescribed.